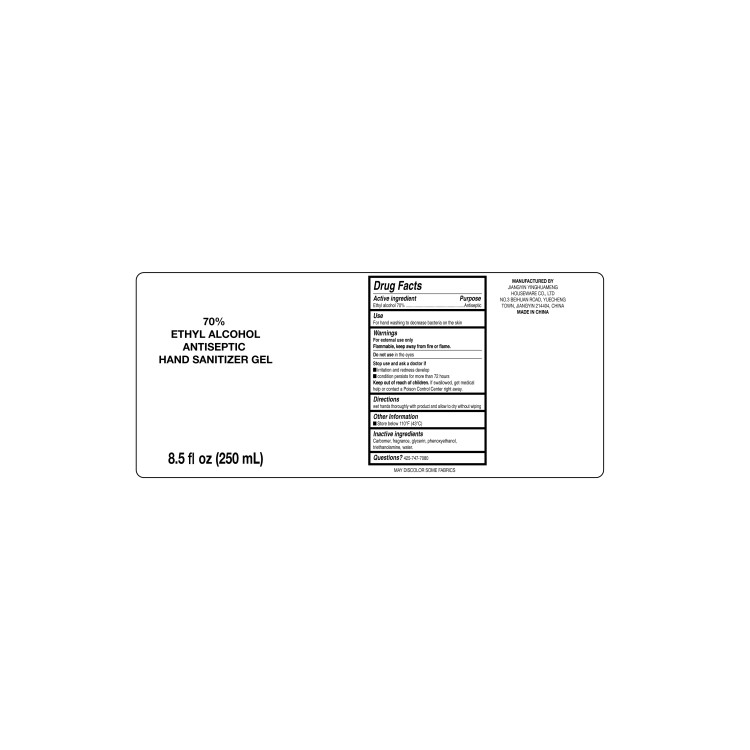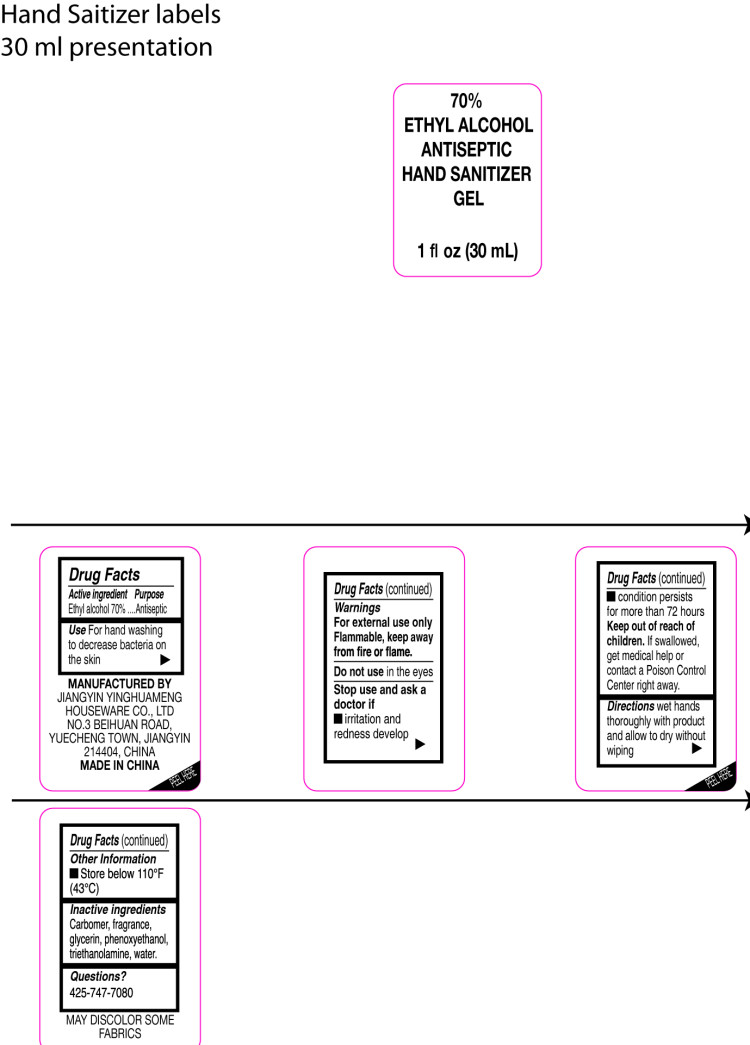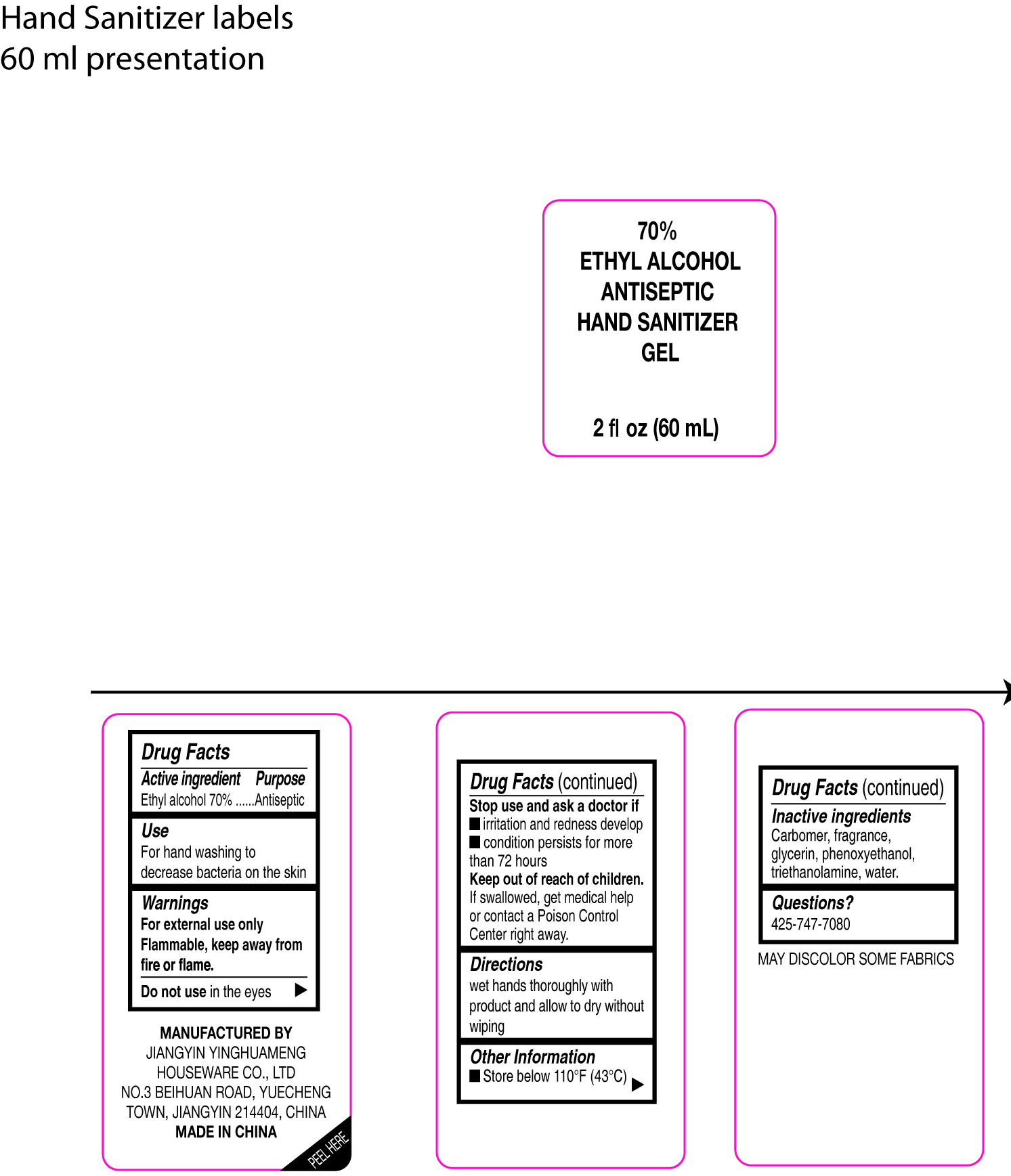 DRUG LABEL: Hand sanitizer
NDC: 75126-015 | Form: GEL
Manufacturer: Jiangyin Yinghuameng Houseware Co., Ltd.
Category: otc | Type: HUMAN OTC DRUG LABEL
Date: 20200808

ACTIVE INGREDIENTS: ALCOHOL 70 mL/100 mL
INACTIVE INGREDIENTS: CARBOMER HOMOPOLYMER, UNSPECIFIED TYPE; GLYCERIN; TROLAMINE; PHENOXYETHANOL; WATER

HAND SANITIZER 015

Active Ingredient

Ethyl Alcohol 70%.

Purpose

Antiseptic

Use

For hand washing to decrease bacteria on the skin

Warnings

For external use only
Flammable, keep away from fire or flame.

Do not use in the eyes

Stop use and ask a doctor if
irritation and redness develop
condition persists for more than 72 hours

Keep out of reach of children

If swallowed, get medical help or contact a Poison Control Center right away.

Directions

Wet hands thoroughly with product and allow to dry without wiping

Other Information

Store below 106°F.(41℃)

May discolor certain fabrics or surfaces

INACTIVE INGREDIENTS

Carbomer, fragrance, glycerin, phenoxyethanol,
triethanolamine, water.